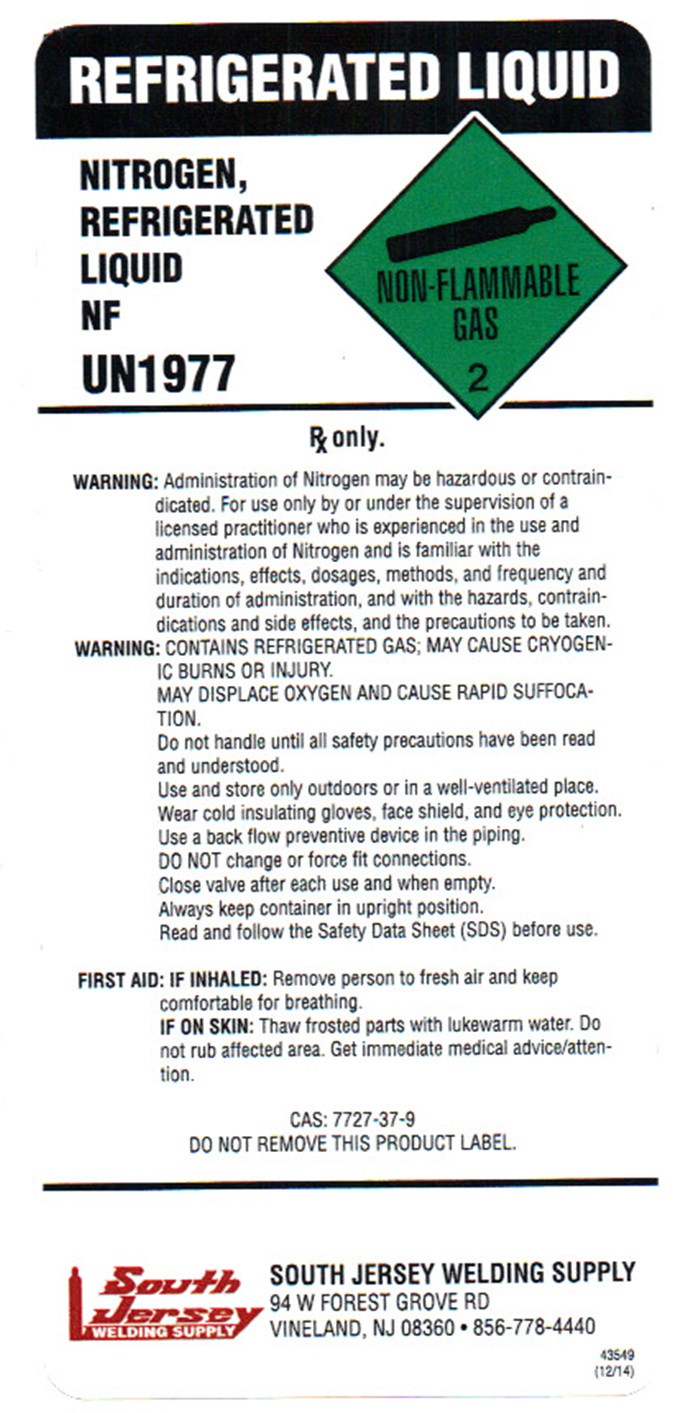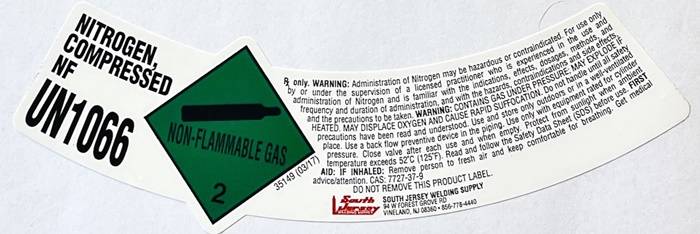 DRUG LABEL: NITROGEN
NDC: 11056-010 | Form: GAS
Manufacturer: South Jersey Welding Supply
Category: prescription | Type: HUMAN PRESCRIPTION DRUG LABEL
Date: 20241028

ACTIVE INGREDIENTS: NITROGEN 99 L/100 L

NITROGEN COMPRESSED NF Label

NITROGEN COMPRESSED NF

UN 1066

NON-Flammable Gas 2

35149 (03-17)

Rx only. WARNING: Administration of Nitrogen may be hazardous or contraindicated. For use only by or under the supervision of a licensed practitioner who is experienced in the use and administration of Nitrogen and is familiar with the indications, effects, dosages, methods, and frequency and duration of administration, and with the hazards, contraindications, and side effects and the precautions to be taken.

WARNING: CONTAINS GAS UNDER PRESSURE; MAY EXPLODE IF HEATED. MAY DISPLACE OXYGEN AND CAUSE RAPID SUFFOCATION. Do not handle until all safety precautions have been read and understood. Use and store only out doors or in a well-ventilated place. Use a backflow preventative device in the piping. Close valve after each use and when empty. Protect from sunlight when the ambient temperature exceeds 52°C (125°F). Read and follow the Safety Data Sheet (SDS) before each use.

FIRST AID: IF INHALED: Remove person to fresh air and keep comfortable for breathing. Get medical advice/attention. CAS: 7727-37-9

DO NOT REMOVE THIS PRODUCT LABEL

SOUTH JERSEY WELDING SUPPLY

94 W FOREST GROVE RD

VINELAND, NJ 08360•856-778-4440

NITROGEN REFRIGERATED LIQUID NF Label

REFRIGERATED LIQUID

NITROGEN REFRIGERATED LIQUID NF

UN1977

NON-FLAMMABLE GAS 2

RX ONLY.

WARNING: Administration of Nitrogen may be hazardous or contraindicated. For use only by or under the supervision of a licensed practitioner who is experienced in the use and administration of Nitrogen and is familiar with the indications, effects, dosages, methods, and frequency and duration of administration, and with the hazards, contraindications, and side effects and the precautions to be taken.

WARNING: CONTAINS REFRIGERATED GAS: MAY CAUSE CRYOGENIC BURNS OR INJURY.

MAY DISPLACE OXYGEN AND CAUSE RAPID SUFFOCATION.

Do not handle until all safety precautions have been read and understood

Use and store only outdoors or in a well-ventilated place.

Wear cold insulating gloves, face shield, and eye protection.

Use a back flow preventive device in the piping.

DO NOT change or force fit connections.

Close valve after each use and when empty.

Always keep container in upright posititon.

Read and follow the Safety Data Sheet (SDS) before use.

FIRST AID: IF INHALED: Remove person to fresh air and keep cmpoortable for breathing.

IF ON SKIN: Thaw frosted parts with lukewarm water. Do not rub affected area. Get immediate medical advice/attention.

CAS: 7727-37-9

DO NOT REMOVE THIS PRODUCT LABEL

SOUTH JERSEY WELDING SUPPLY

94 W FOREST GROVE RD

VINELAND, NJ 08360•856-778-4440

43549 (12/14)